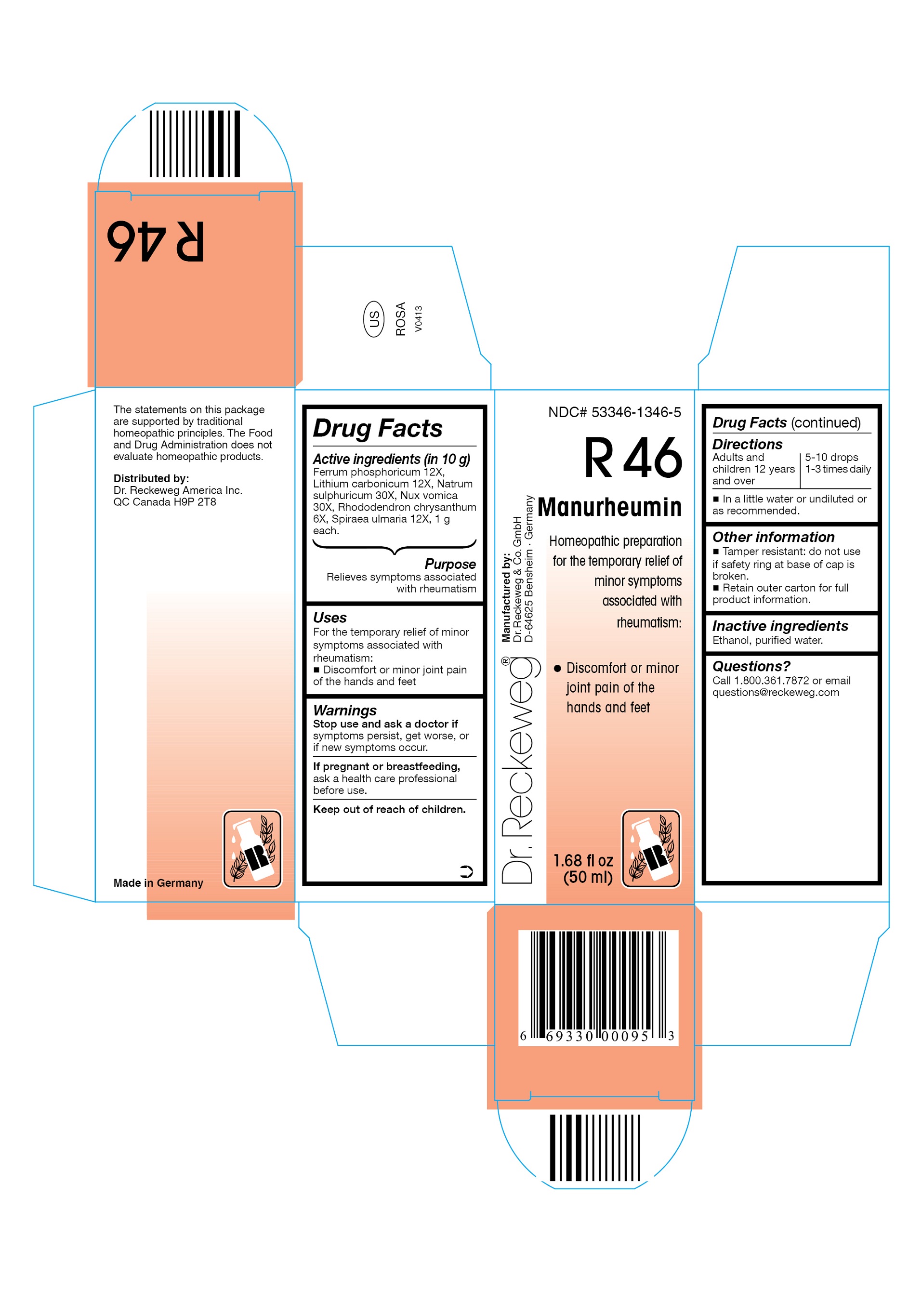 DRUG LABEL: DR. RECKEWEG R46 Manurheumin
NDC: 53346-1346 | Form: LIQUID
Manufacturer: PHARMAZEUTISCHE FABRIK DR. RECKEWEG & CO
Category: homeopathic | Type: HUMAN OTC DRUG LABEL
Date: 20130405

ACTIVE INGREDIENTS: FERRIC PHOSPHATE 12 [hp_X]/50 mL; LITHIUM CARBONATE 12 [hp_X]/50 mL; SODIUM SULFATE 30 [hp_X]/50 mL; STRYCHNOS NUX-VOMICA SEED 30 [hp_X]/50 mL; RHODODENDRON AUREUM LEAF 6 [hp_X]/50 mL; FILIPENDULA ULMARIA ROOT 12 [hp_X]/50 mL
INACTIVE INGREDIENTS: ALCOHOL; WATER

DR. RECKEWEG R46 Manurheumin

Active ingredients

Ferrum phosphoricum 12X, Lithium carbonicum 12X, Natrum sulphuricum 30X, Nux vomica 30X, Rhododendron chrysanthum 6X, Spiraea ulmaria 12X, 1 g each in 10 g.

Purpose

Relieves symptoms associated with rheumatism

Uses

For the temporary relief of minor symptoms associated with rheumatism:

- Discomfort or minor joint pain of the hands and feet

Warnings

Stop use and ask a doctor if symptoms persist, get worse, or if new symptoms occur.

PREGNANCY OR BREAST FEEDING

If pregnant or breastfeeding, ask a health care professional before use.

Keep out of reach of children.

Directions

Adults and children ≥ 12 years 5-10 drops 1-3 times daily in a little water or undiluted or as recommended.

Other information

- Tamper resistant: do not use if safety ring at base of cap is broken.
- Retain outer carton for full product information.

Inactive ingredients

Ethanol, purified water.

Questions?
Call 1-800-361-7872 or email questions@reckeweg.com

PACKAGE LABEL

NDC# 53346-1346-5

Dr. Reckeweg R46 Manurheumin

Homeopathic preparation for the temporary relief of minor symptoms associated with rheumatism:

- Discomfort or minor joint pain of the hands and feet

Manufactured by:

Dr. Reckeweg Co. GmbH

D-64625 Bensheim

Germany

1.68 fl oz
(50 ml)